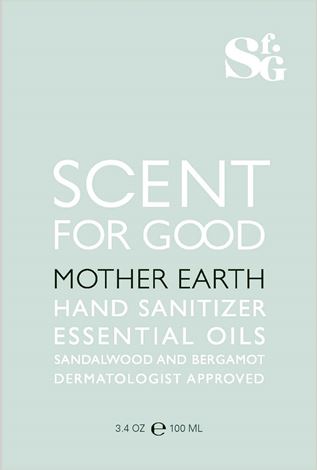 DRUG LABEL: SCENT FOR GOOD HAND SANITIZER
NDC: 80384-001 | Form: GEL
Manufacturer: SCENT FOR GOOD LLC
Category: otc | Type: HUMAN OTC DRUG LABEL
Date: 20230221

ACTIVE INGREDIENTS: ALCOHOL 60 g/100 mL
INACTIVE INGREDIENTS: WATER; METHYL GLUCETH-20; GLYCERETH-7 TRIACETATE; GLYCERIN; ALOE VERA LEAF; HYDROLYZED JOJOBA ESTERS (ACID FORM); CARBOMER INTERPOLYMER TYPE A (ALLYL SUCROSE CROSSLINKED); AMINOMETHYLPROPANOL

SCENT FOR GOOD HAND SANITIZER

ACTIVE INGREDIENT:

ETHYL ALCOHOL 60%

PURPOSE:

ANTIMICROBIAL

USE:

YES, PLEASE. ESPECIALLY WHEN SOAP AND WATER ARE NOT AVAILABLE. THIS PRODUCT HELPS REDUCE BACTERIA ON YOUR SKIN.

WARNINGS:

FOR EXTERNAL USE ONLY. FLAMMABLE. KEEP AWAY FROM HEAT OR FLAME.

DO NOT USE

ON CHILDREN LESS THAN 2 MONTHS OF AGE OR ON OPEN SKIN WOUNDS.

WHEN USING THIS PRODUCT

KEEP OUT OF EYES, EARS, AND MOUTH. IN CASE OF CONTACT WITH EYES, RINSE EYES THOROUGHLY WITH WATER.

STOP USE AND ASK A DOCTOR

IF IRRITATION OR RASH OCCURS. THESE MAY BE SIGNS OF A SERIOUS CONDITION.

KEEP OUT OF REACH OF CHILDREN.

IF SWALLOWED, GET MEDICAL HELP OR CONTACT A POISON CONTROL CENTER IMMEDIATELY.

DIRECTIONS:

DON’T BE SHY, BE SAFE. PLACE ENOUGH PRODUCT IN PALM TO COVER HANDS. RUB TOGETHER UNITL DRY. SUPERVISE CHILDREN UNDER 6 YEARS OF AGE WHEN USING. THANK YOU, PLEASE.

OTHER INFORMATION:

STORE BETWEEN 15o-30o C (59o-86o F). AVOID FREEZING AND EXCESSIVE HEAT ABOVE 40oC (104oF). MAY DISCOLOR CERTAIN FABRICS OR SURFACES.

INACTIVE INGREDIENTS:

WATER (AQUA), METHYL GLUCETH-20, FRAGRANCE (PARFUM), GLYCERETH-7 TRIACETATE, GLYCERIN, ALOE BARBADENSIS LEAF JUICE, HYDROLYZED JOJOBA ESTERS, ACRYLATES/C10-30 ALKYL ACRYLATE CROSSPOLYMER, AMINOMETHYL PROPANOL

PACKAGE/LABEL PRINCIPAL DISPLAY PANEL

Sf. G

SCENT
FOR GOOD
MOTHER EARTH
HAND SANITIZER
ESSENTIAL OILS
SANDALWOOD AND BERGAMOT
DERMATOLOGIST APPROVED

3.4 OZ ℮ 100 ML

NDC 80384-001-01
7Y57200 FDA, SANITIZER, HAND KARMA
Manufactured by FMI for Scent for Good, New York, NY 10011
scentforgood.com @scentforgood

Label